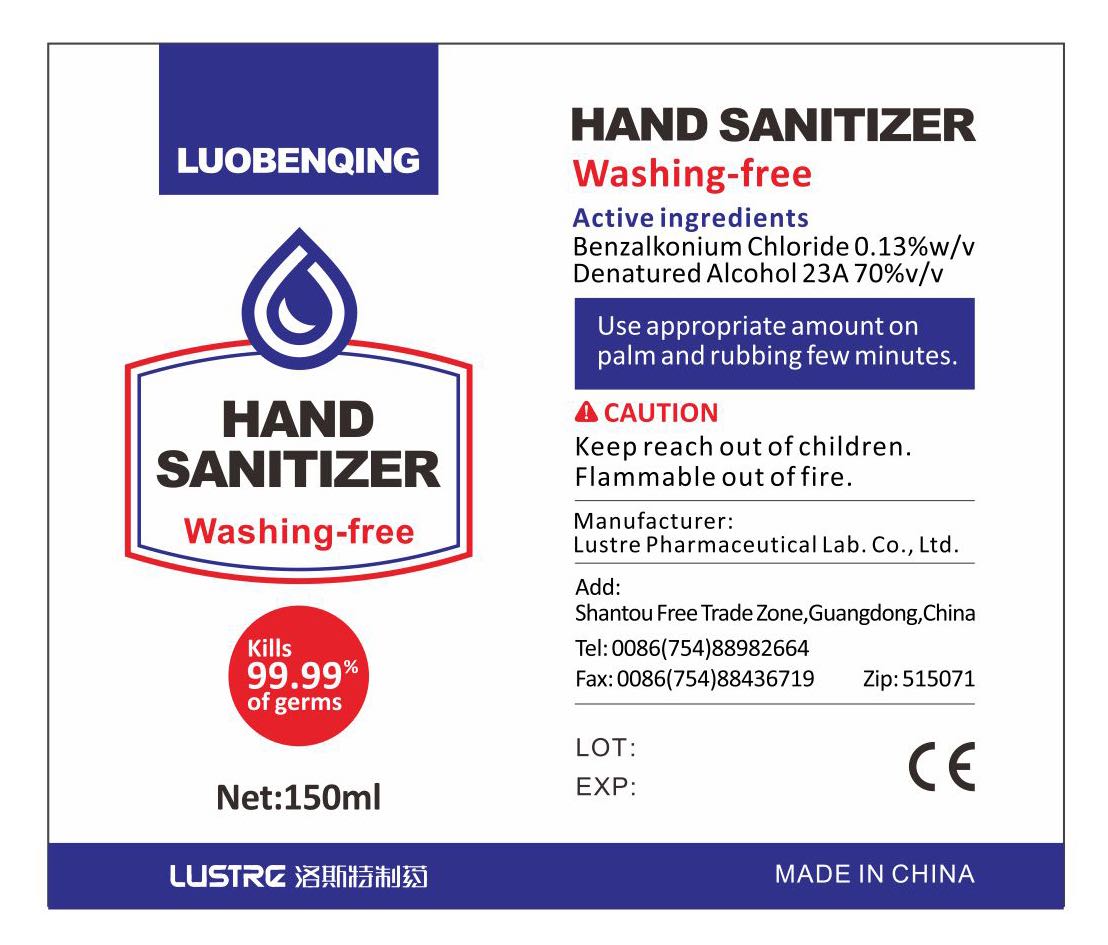 DRUG LABEL: luobenqing HAND SANITIZER
NDC: 53042-003 | Form: LIQUID
Manufacturer: LUSTRE Pharmaceutical Lab.Co.,Ltd.
Category: otc | Type: HUMAN OTC DRUG LABEL
Date: 20200409

ACTIVE INGREDIENTS: ALCOHOL 105 mL/150 mL; BENZALKONIUM CHLORIDE 0.195 mg/150 mL
INACTIVE INGREDIENTS: WATER

DOSAGE AND ADMINISTRATION

Flammable out of fire.

ACTIVE INGREDIENT

Benzalkonium Chloride 0.1 3%w/v
Denatured Alcohol 23A 70%v/v

INACTIVE INGREDIENT

water

PURPOSE

Disinfection
Sterilization
No Rinseing

INDICATIONS AND USAGE

Use appropriate amount on palm and rubbing few minutes.

WARNINGS

Keep reach out of children.
Flammable out of fire.

keep out of reach of children